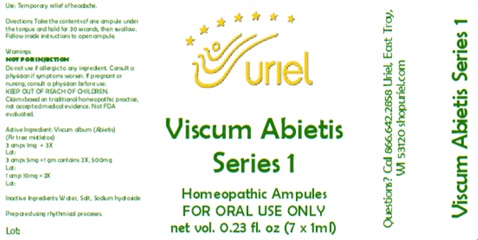 DRUG LABEL: Viscum Abietis Series 1 7ml
NDC: 48951-9242 | Form: LIQUID
Manufacturer: Uriel Pharmacy Inc.
Category: homeopathic | Type: HUMAN OTC DRUG LABEL
Date: 20260203

ACTIVE INGREDIENTS: VISCUM ALBUM FRUITING TOP 2 [hp_X]/1 mL
INACTIVE INGREDIENTS: WATER; SODIUM CHLORIDE; SODIUM HYDROXIDE

Viscum Abietis Series 1 7ml

PURPOSE

Use: Temporary relief of headache.

INDICATIONS AND USAGE

FOR ORAL USE ONLY

DOSAGE AND ADMINISTRATION

Directions: Take the contents of one ampule under the tongue and hold for 30 seconds, then swallow. Follow inside instructions to open ampule.

Warnings:
NOT FOR INJECTION
Do not use if allergic to any ingredient. Consult a physician if symptoms worsen. If pregnant or nursing, consult a physician before use.
Claims based on traditional homeopathic practice, not accepted medical evidence. Not FDA evaluated.

KEEP OUT OF REACH OF CHILDREN.

Active Ingredient: Viscum Abietis (Fir tree mistletoe)
3 amps 1mg = 3X
3 amps 5mg = 1 gm contains: 2X, 500mg
1 amp 10mg = 2X

Inactive Ingredients: Water, Salt, Sodium Hydroxide

Prepared using rhythmical processes.

QUESTIONS

Questions? Call 866.642.2858 Uriel, East Troy, WI 53120 shopuriel.com Lot: